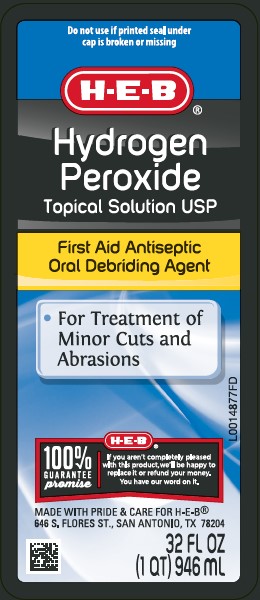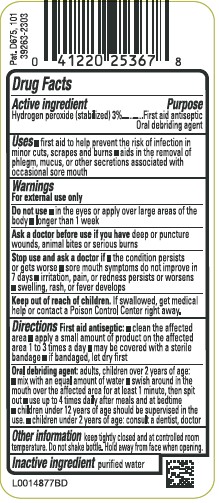 DRUG LABEL: Hydrogen Peroxide
NDC: 37808-871 | Form: SOLUTION
Manufacturer: H E B
Category: otc | Type: HUMAN OTC DRUG LABEL
Date: 20260224

ACTIVE INGREDIENTS: HYDROGEN PEROXIDE 30 mg/1 mL
INACTIVE INGREDIENTS: WATER

HEB 871.001/871AA
3% Hydrogen Peroxide

Active ingredient

Hydrogen peroxide (stabilized) 3%

Purpose

First aid antiseptic

Oral debriding agent

Uses

- first aid to help prevent the risk of infection in minor cuts, scrapes and burns
- aids in the removal of phlegm, mucus, or other secretions associated with occasional sore mouth

Warnings

For external use only

Do not use

- in the eyes or apply over large areas of the body
- longer than 1 week

Ask a doctor before use if you have

deep or pucture wounds, animal bites or serious burns

Stop use and ask a doctor if

- the condition persists or gets worse
- sore mouth symptoms do not improve in 7 days
- irritation, pain, or redness persists or worsens
- swelling, rash, or fever develops

Keep out of reach of children.

If swallowed, get medical help or contact a Poison Control Center right away.

Directions

First Aid Antiseptic:

- clean the affected area
- apply a small amount of the product on the affected area 1 to 3 times a day
- may be covered with a sterile bandage
- if bandaged, let dry first

Oral Debriding Agent: adults, children over 2 years of age:

- mix with equal amount of water
- swish around in the mouth over the affected area for at least 1 minute, then spit out
- use up to 4 times daily after meals and at bedtime
- children under 12 years of age should be supervised in the use
- children under 2 years of age: consult a dentist or doctor

Other information

Keep tightly closed and at controlled room temperature. Do not shake bottle. Hold away from face when opening.

Inactive ingredient

purified water

Principal display panel

Do not use if printed seal under cap is broken or missing

H-E-B®

Hydrogen Peroxide

Topical Solution USP

First Aid Antiseptic

Oral Debriding Agent

- For Treatment of Minor Cuts and Abrasions

H-E-B®

100 % GUARANTEE PROMISE

If you aren't completely pleased with this product, we'll be happy to replace it or refund your money. You have our word on it.

MADE WITH PRIDE & CARE FOR H-E-B®

646 S. FLORES ST., SAN ANTONIO, TX 78204

32 FL OZ (1 QT) 946 mL